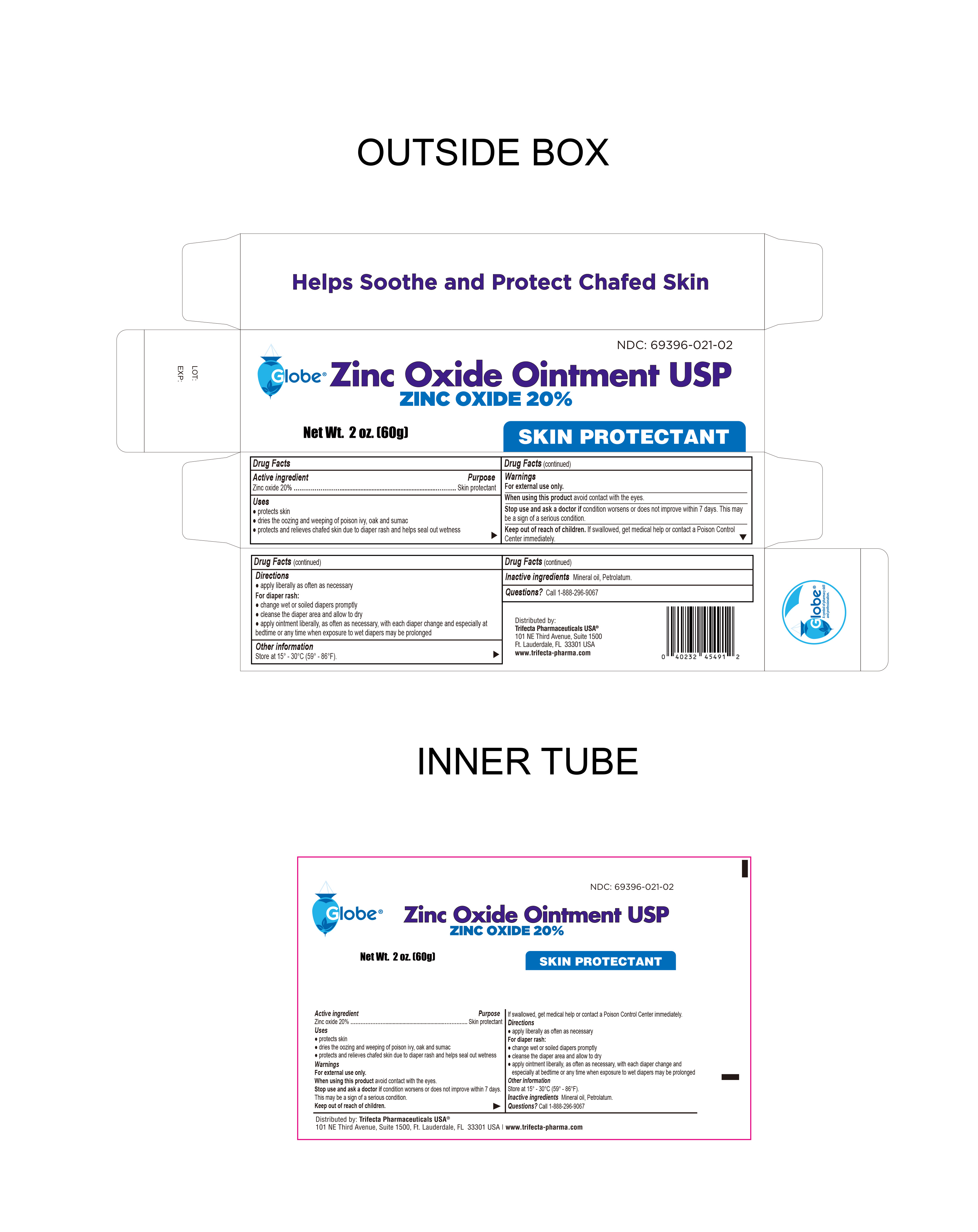 DRUG LABEL: Zinc Oxide 20%
NDC: 69396-021 | Form: OINTMENT
Manufacturer: Trifecta Pharmaceuticals USA
Category: otc | Type: HUMAN OTC DRUG LABEL
Date: 20251201

ACTIVE INGREDIENTS: ZINC OXIDE 0.2 g/1 g
INACTIVE INGREDIENTS: MINERAL OIL; PETROLATUM

Zinc Oxide Ointment 20%

Active Ingredient

Zinc Oxide 20%

Purpose

Skin Protectant

Uses

- Protects skin
- Protects and releives chafed skin due to diaper rash - helps seal out wetness
- Dries the oozing and weeping of poison ivy, oak and sumac

Keep out of the reach of children

If swallowed, get medical help or contact a Poison Control Center immediately.

Warnings

For External Use Only

- When using this product avoid contact with eyes
- Stop use and ask a doctor if condition worsens or does not improve within 7 days. This may be a sign of a serious condition.

Directions

- Apply ointment liberally as often as necessary
- For the treatment of diaper rash, change wet and soiled diapers promptly
- Cleanse the diaper area and allow to dry
- Apply with each diaper change, especially at bedtime or anytime when exposure to wet diaper may be prolonged

Other Information

- Store at controlled room temperature 15° - 30°C (59° - 86°F)

Inactive Ingredients

Mineral Oil, Petrolatum

Distributed By:

Trifecta Pharmaceuticals USA, LLC.

101 NE Third Avenue, Ste. 1500

Ft. Lauderdale, FL. 33301, USA.

Product of PRC

www.trifecta-pharma.com